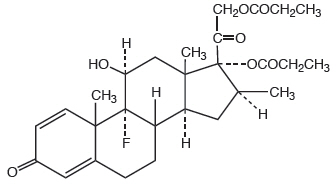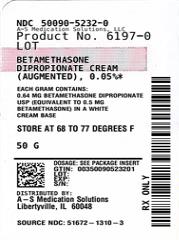 DRUG LABEL: Betamethasone Dipropionate
NDC: 50090-5232 | Form: CREAM, AUGMENTED
Manufacturer: A-S Medication Solutions
Category: prescription | Type: HUMAN PRESCRIPTION DRUG LABEL
Date: 20260206

ACTIVE INGREDIENTS: BETAMETHASONE DIPROPIONATE 0.5 mg/1 g
INACTIVE INGREDIENTS: CARBOMER 940; CETEARETH-30; P-CHLORO-M-CRESOL; CYCLOPENTASILOXANE; GLYCERYL OLEATE; PROPYLENE GLYCOL; AQUA; SODIUM HYDROXIDE; SORBITOL; PETROLATUM; WHITE WAX

HIGHLIGHTS OF PRESCRIBING INFORMATION

These highlights do not include all the information needed to use BETAMETHASONE DIPROPIONATE CREAM (augmented) safely and effectively. See full prescribing information for BETAMETHASONE DIPROPIONATE CREAM (augmented).
BETAMETHASONE DIPROPIONATE cream, for topical use
Initial U.S. Approval: 1983

1 INDICATIONS AND USAGE

Betamethasone dipropionate cream (augmented), 0.05% is a corticosteroid indicated for the relief of the inflammatory and pruritic manifestations of corticosteroid-responsive dermatoses in patients 13 years of age and older. (1)

2 DOSAGE AND ADMINISTRATION

- Apply a thin film to the affected skin areas once or twice daily. (2)
- Discontinue therapy when control is achieved. (2)
- Use no more than 50 g per week. (2)
- Do not use with occlusive dressings unless directed by a physician. (2)
- Avoid use on the face, groin, or axillae, or if skin atrophy is present at the treatment site. (2)
- Not for oral, ophthalmic, or intravaginal use. (2)

3 DOSAGE FORMS AND STRENGTHS

- Cream, 0.05% (3)

4 CONTRAINDICATIONS

- Hypersensitivity to any component of this medicine. (4)

5 WARNINGS AND PRECAUTIONS

- Effects on endocrine system: Betamethasone dipropionate cream (augmented) can cause reversible HPA axis suppression with the potential for glucocorticosteroid insufficiency during and after withdrawal of treatment. Risk factor(s) include the use of high-potency topical corticosteroids, use over a large surface area or to areas under occlusion, prolonged use, altered skin barrier, liver failure, and use in pediatric patients. Modify use should HPA axis suppression develop. (5.1, 8.4)
- Ophthalmic Adverse Reactions: Betamethasone dipropionate cream (augmented) may increase the risk of cataracts and glaucoma. If visual symptoms occur, consider referral to an ophthalmologist for evaluation. (5.2)

6 ADVERSE REACTIONS

- The most common adverse reaction reported in 0.4% of adult patients is stinging. (6.1)
- The most common adverse reactions reported in 10% of pediatric patients are signs of skin atrophy, telangiectasia, bruising, shininess. (6.1, 8.4)

To report SUSPECTED ADVERSE REACTIONS, contact Sun Pharmaceutical Industries, Inc., at 1-866-923-4914 or FDA at 1-800-FDA-1088 or www.fda.gov/medwatch.

FULL PRESCRIBING INFORMATION

1 INDICATIONS AND USAGE

Betamethasone dipropionate cream (augmented) is a corticosteroid indicated for the relief of the inflammatory and pruritic manifestations of corticosteroid-responsive dermatoses in patients 13 years of age or older.

2 DOSAGE AND ADMINISTRATION

Apply a thin film of betamethasone dipropionate cream (augmented) to the affected skin areas once or twice daily.

Therapy should be discontinued when control is achieved. Betamethasone dipropionate cream (augmented) is a high-potency corticosteroid. Treatment with betamethasone dipropionate cream (augmented) should not exceed 50 g per week because of the potential for the drug to suppress the hypothalamic-pituitary-adrenal (HPA) axis [see Warnings and Precautions (5.1)].

Betamethasone dipropionate cream (augmented) should not be used with occlusive dressings unless directed by a physician.

Avoid contact with eyes. Wash hands after each application.

Avoid use on the face, groin, or axillae, or if skin atrophy is present at the treatment site.

Betamethasone dipropionate cream (augmented) is for topical use only. It is not for oral, ophthalmic, or intravaginal use.

3 DOSAGE FORMS AND STRENGTHS

Cream, 0.05%. Each gram of betamethasone dipropionate cream USP (augmented), 0.05% contains 0.64 mg betamethasone dipropionate (equivalent to 0.5 mg betamethasone) in a white cream base.

4 CONTRAINDICATIONS

Betamethasone dipropionate cream (augmented), is contraindicated in patients who are hypersensitive to betamethasone dipropionate, to other corticosteroids, or to any ingredient in this preparation.

5 WARNINGS AND PRECAUTIONS

5.1 Effects on Endocrine System

Betamethasone dipropionate cream (augmented) can produce reversible hypothalamic-pituitary-adrenal (HPA) axis suppression with the potential for glucocorticosteroid insufficiency. This may occur during treatment or after withdrawal of treatment. Factors that predispose to HPA axis suppression include the use of high-potency steroids, large treatment surface areas, prolonged use, use of occlusive dressings, altered skin barrier, liver failure, and young age. Evaluation for HPA axis suppression may be done by using the adrenocorticotropic hormone (ACTH) stimulation test.

Betamethasone dipropionate cream (augmented), 0.05% was applied once daily at 7 grams per day for 1 week to diseased skin, in adult subjects with psoriasis or atopic dermatitis, to study its effects on the HPA axis. The results suggested that the drug lowered adrenal corticosteroid secretion, although plasma cortisol levels did not go below the lower limit of the normal range.

In an open-label pediatric trial of 60 evaluable subjects (3 months to 12 years of age), 19 subjects showed evidence of HPA axis suppression. Four (4) subjects were tested 2 weeks after discontinuation of betamethasone dipropionate cream (augmented), 0.05%, and 3 of the 4 (75%) had complete recovery of HPA axis function. The proportion of subjects with adrenal suppression in this trial was progressively greater, the younger the age group.

If HPA axis suppression is documented, gradually withdraw the drug, reduce the frequency of application, or substitute with a less potent corticosteroid. Infrequently, signs and symptoms of steroid withdrawal may occur, requiring supplemental systemic corticosteroids.

Cushing's syndrome and hyperglycemia may also occur with topical corticosteroids. These events are rare and generally occur after prolonged exposure to excessively large doses, especially of high-potency topical corticosteroids.

Pediatric patients may be more susceptible to systemic toxicity due to their larger skin surface to body mass ratios [see Use in Specific Populations (8.4)].

5.2 Ophthalmic Adverse Reactions

Use of topical corticosteroids, including betamethasone dipropionate cream (augmented), may increase the risk of posterior subcapsular cataracts and glaucoma. Cataracts and glaucoma have been reported postmarketing with the use of topical corticosteroid products, including betamethasone dipropionate cream (augmented) [see Adverse Reactions (6.2)] .

5.3 Allergic Contact Dermatitis

Allergic contact dermatitis with corticosteroids is usually diagnosed by observing failure to heal rather than noting a clinical exacerbation. Such an observation should be corroborated with appropriate diagnostic patch testing. If irritation develops, topical corticosteroids should be discontinued and appropriate therapy instituted.

6 ADVERSE REACTIONS

6.1 Clinical Trials Experience

Because clinical trials are conducted under widely varying conditions, adverse reaction rates observed in the clinical trials of a drug cannot be directly compared to rates in the clinical trials of another drug and may not reflect the rates observed in clinical practice.

In controlled clinical trials, involving 242 adult subjects, the adverse reaction associated with the use of betamethasone dipropionate cream (augmented) reported at a frequency of 0.4% was stinging. It occurred in 1 subject.

In a controlled clinical trial involving 67 pediatric subjects from 3 months to 12 years of age, the adverse reactions associated with the use of betamethasone dipropionate cream (augmented) occurred in 7 of 67 (10%) subjects. Reported reactions included signs of skin atrophy (telangiectasia, bruising, shininess).

6.2 Postmarketing Experience

Because adverse reactions are reported voluntarily from a population of uncertain size, it is not always possible to reliably estimate their frequency or establish a causal relationship to drug exposure.

Postmarketing reports for local adverse reactions to topical corticosteroids may also include: burning, itching, irritation, dryness, folliculitis, acneiform eruptions, hypopigmentation, perioral dermatitis, allergic contact dermatitis, secondary infection, hypertrichosis, skin atrophy, striae, and miliaria.

Hypersensitivity reactions, consisting of predominantly skin signs and symptoms, e.g., contact dermatitis, pruritus, bullous dermatitis, and erythematous rash have been reported.

Ophthalmic adverse reactions of cataracts, glaucoma, increased intraocular pressure, and central serous chorioretinopathy have been reported with the use of topical corticosteroids, including topical betamethasone products.

8 USE IN SPECIFIC POPULATIONS

8.1 Pregnancy

Risk Summary

There are no available data on betamethasone dipropionate cream (augmented) use in pregnant women to identify a drug-associated risk of major birth defects, miscarriage, or adverse maternal or fetal outcomes.

Observational studies suggest an increased risk of low birthweight infants with the use of greater than 300 grams of potent or very potent topical corticosteroid during a pregnancy. Advise pregnant women that betamethasone dipropionate cream (augmented) may increase the risk of having a low birthweight infant and to use betamethasone dipropionate cream (augmented) on the smallest area of skin and for the shortest duration possible.

In animal reproduction studies, increased malformations, including umbilical hernias, cephalocele, and cleft palate, were observed after intramuscular administration of betamethasone dipropionate to pregnant rabbits. The available data do not allow the calculation of relevant comparisons between the systemic exposure of betamethasone dipropionate in animal studies to the systemic exposure that would be expected in humans after topical use of betamethasone dipropionate cream (augmented) (see Data) .

The background risk of major birth defects and miscarriage for the indicated population is unknown. All pregnancies have a background risk of birth defect, loss, or other adverse outcomes. In the U.S. general population, the estimated risk of major birth defects and miscarriage in clinically recognized pregnancies is 2 to 4% and 15 to 20%, respectively.

Data

Animal Data

Betamethasone dipropionate has been shown to cause malformations in rabbits when given by the intramuscular route at doses of 0.05 mg/kg. The abnormalities observed included umbilical hernias, cephalocele, and cleft palate.

8.2 Lactation

Risk Summary

There are no data regarding the excretion of betamethasone dipropionate in breast milk, the effects on the breastfed infant, or the effects on milk production after topical application of betamethasone dipropionate cream (augmented) to women who are breastfeeding.

It is possible that topical administration of large amounts of betamethasone dipropionate could result in sufficient systemic absorption to produce detectable quantities in human milk. The developmental and health benefits of breastfeeding should be considered along with the mother's clinical need for betamethasone dipropionate cream (augmented) and any potential adverse effects on the breastfed infant from betamethasone dipropionate cream (augmented) or from the underlying maternal condition.

Clinical Considerations

To minimize potential exposure to the breastfed infant via breast milk, use betamethasone dipropionate cream (augmented) on the smallest area of skin and for the shortest duration possible while breastfeeding. Advise breastfeeding women not to apply betamethasone dipropionate cream (augmented) directly to the nipple and areola to avoid direct infant exposure [see Use in Specific Populations (8.4)] .

8.4 Pediatric Use

Use of betamethasone dipropionate cream (augmented) in pediatric patients younger than 13 years of age is not recommended due to the potential for HPA axis suppression [see Warnings and Precautions (5.1)] .

In an open-label HPA axis safety trial in subjects 3 months to 12 years of age with atopic dermatitis, betamethasone dipropionate cream (augmented), 0.05% was applied twice daily for 2 to 3 weeks over a mean body surface area of 58% (range 35% to 95%). In 19 of 60 (32%) evaluable subjects, adrenal suppression was indicated by either a ≤5 mcg/dL pre-stimulation cortisol, or a cosyntropin post-stimulation cortisol ≤18 mcg/dL and/or an increase of <7 mcg/dL from the baseline cortisol. Out of the 19 subjects with HPA axis suppression, 4 subjects were tested 2 weeks after discontinuation of betamethasone dipropionate cream (augmented), and 3 of the 4 (75%) had complete recovery of HPA axis function. The proportion of subjects with adrenal suppression in this trial was progressively greater, the younger the age group.

Because of a higher ratio of skin surface area to body mass, pediatric patients are at a greater risk than adults of systemic toxicity when treated with topical drugs. They are, therefore, also at greater risk of HPA axis suppression and adrenal insufficiency upon the use of topical corticosteroids.

Rare systemic effects such as Cushing's syndrome, linear growth retardation, delayed weight gain, and intracranial hypertension have been reported in pediatric patients, especially those with prolonged exposure to large doses of high potency topical corticosteroids.

Local adverse reactions including skin atrophy have also been reported with use of topical corticosteroids in pediatric patients.

Avoid use of betamethasone dipropionate cream (augmented) in the treatment of diaper dermatitis.

8.5 Geriatric Use

Clinical trials of betamethasone dipropionate cream (augmented) included 104 subjects who were 65 years of age and over and 8 subjects who were 75 years of age and over. No overall differences in safety or effectiveness were observed between these subjects and younger subjects, and other reported clinical experience has not identified differences in responses between the elderly and younger patients. However, greater sensitivity of some older individuals cannot be ruled out.

11 DESCRIPTION

Betamethasone dipropionate cream USP (augmented), 0.05% contains betamethasone dipropionate USP, a synthetic adrenocorticosteroid, for topical use in a cream base. Betamethasone, an analog of prednisolone, has a high degree of corticosteroid activity and a slight degree of mineralocorticoid activity. Betamethasone dipropionate is the 17,21-dipropionate ester of betamethasone.

Chemically, betamethasone dipropionate is 9-fluoro-11β,17,21-trihydroxy-16β-methylpregna-1,4-diene-3,20-dione 17,21-dipropionate, with the empirical formula C28H37FO7, a molecular weight of 504.6, and the following structural formula:

Betamethasone dipropionate is a white to creamy white, odorless crystalline powder, insoluble in water.

Each gram of betamethasone dipropionate cream USP (augmented), 0.05% contains: 0.64 mg betamethasone dipropionate USP (equivalent to 0.5 mg betamethasone) in a white cream base of carbomer homopolymer type C, ceteareth-30, chlorocresol, cyclomethicone, glyceryl oleate, propylene glycol, purified water, sodium hydroxide, sorbitol solution, white petrolatum and white wax.

12 CLINICAL PHARMACOLOGY

12.1 Mechanism of Action

Corticosteroids play a role in cellular signaling, immune function, inflammation, and protein regulation; however, the precise mechanism of action of betamethasone dipropionate cream (augmented) in corticosteroid responsive dermatoses is unknown.

12.2 Pharmacodynamics

Vasoconstrictor Assay

Trials performed with betamethasone dipropionate cream (augmented), 0.05% indicate that it is in the high range of potency as demonstrated in vasoconstrictor trials in healthy subjects when compared with other topical corticosteroids. However, similar blanching scores do not necessarily imply therapeutic equivalence.

12.3 Pharmacokinetics

No pharmacokinetics trials have been conducted with betamethasone dipropionate cream (augmented), 0.05%. The extent of percutaneous absorption of topical corticosteroids is determined by many factors including the vehicle, the integrity of the epidermal barrier, and the use of occlusive dressings.

Topical corticosteroids can be absorbed through normal intact skin. Inflammation and/or other disease processes in the skin may increase percutaneous absorption. Occlusive dressings substantially increase the percutaneous absorption of topical corticosteroids [see Dosage and Administration (2)] .

Once absorbed through the skin, topical corticosteroids enter pharmacokinetic pathways similar to systemically administered corticosteroids. Corticosteroids are bound to plasma proteins in varying degrees, are metabolized primarily in the liver, and excreted by the kidneys. Some of the topical corticosteroids and their metabolites are also excreted into the bile.

13 NONCLINICAL TOXICOLOGY

13.1 Carcinogenesis, Mutagenesis, Impairment of Fertility

Long-term animal studies have not been performed to evaluate the carcinogenic potential of betamethasone dipropionate.

Betamethasone was negative in the bacterial mutagenicity assay (Salmonella typhimuriumand Escherichia coli),and in the mammalian cell mutagenicity assay (CHO/HGPRT). It was positive in the in vitrohuman lymphocyte chromosome aberration assay, and equivocal in the in vivomouse bone marrow micronucleus assay.

Studies in rabbits, mice, and rats using intramuscular doses up to 1, 33, and 2 mg/kg, respectively, resulted in dose-related increases in fetal resorptions in rabbits and mice.

14 CLINICAL STUDIES

The safety and efficacy of betamethasone dipropionate cream (augmented) for the treatment of corticosteroid-responsive dermatoses have been established in two randomized and active controlled trials in subjects with chronic plaque psoriasis. A total of 81 subjects who received betamethasone dipropionate cream (augmented) were included in these trials. These trials evaluated betamethasone dipropionate cream (augmented) applied once or twice daily for 14 and 21 days, respectively, on bilateral paired psoriatic lesions. Betamethasone dipropionate cream (augmented) was shown to be effective in relieving the signs and symptoms of chronic plaque psoriasis.

16 HOW SUPPLIED/STORAGE AND HANDLING

Product: 50090-5232

NDC: 50090-5232-0 50 g in a TUBE / 1 in a CARTON

17 PATIENT COUNSELING INFORMATION

Advise the patient to read the FDA-approved patient labeling (Patient Information).

Inform patients of the following:

- Discontinue therapy when control is achieved, unless directed otherwise by the physician.
- Use no more than 50 grams per week.
- Avoid contact with the eyes.
- Advise patients to report any visual symptoms to their healthcare providers.
- Avoid use of betamethasone dipropionate cream (augmented) on the face, underarms, or groin areas unless directed by the physician.
- Do not occlude the treatment area with bandage or other covering, unless directed by the physician.
- Note that local reactions and skin atrophy are more likely to occur with occlusive use, prolonged use or use of higher potency corticosteroids.
- Advise a woman to use betamethasone dipropionate cream (augmented) on the smallest area of skin and for the shortest duration possible while pregnant or breastfeeding. Advise breastfeeding women not to apply betamethasone dipropionate cream (augmented) directly to the nipple and areola to avoid direct infant exposure.

Mfd. by: Sun Pharma Canada Inc., Brampton, Ontario, Canada L6T 1C1

Dist. by: Sun Pharmaceutical Industries, Inc.,Cranbury, NJ 08512

Revised: December 2025
5264297-0925-01 51

Patient Information
Betamethasone Dipropionate
(bay'' ta meth' a sone dye proe' pee oh nate)
Cream (Augmented)

Important information: Betamethasone Dipropionate Cream (Augmented) is for use on skin only. Do not use betamethasone dipropionate cream (augmented) in your eyes, mouth, or vagina.

What is Betamethasone Dipropionate Cream (Augmented)?

Betamethasone dipropionate cream (augmented) is a prescription corticosteroid medicine used on the skin (topical) for the relief of redness, swelling, heat, pain (inflammation) and itching, caused by certain skin problems in people 13 years of age and older.

- Betamethasone dipropionate cream (augmented) should not be used in children under 13 years of age.

Do not use Betamethasone Dipropionate Cream (Augmented) if youare allergic to betamethasone dipropionate or any of the ingredients in betamethasone dipropionate cream (augmented). See the end of this leaflet for a complete list of ingredients in betamethasone dipropionate cream (augmented).

Before using Betamethasone Dipropionate Cream (Augmented), tell your healthcare provider about all of your medical conditions, including if you:

- have had irritation or other skin reaction to a steroid medicine in the past.
- have thinning of the skin (atrophy) at the treatment site.
- have diabetes.
- have adrenal gland problems.
- have liver problems.
- have cataracts or glaucoma.
- are pregnant or plan to become pregnant. It is not known if betamethasone dipropionate cream (augmented) will harm your unborn baby. If you use betamethasone dipropionate cream (augmented) during pregnancy, use betamethasone dipropionate cream (augmented) on the smallest area of the skin and for the shortest time needed.
- are breastfeeding or plan to breastfeed. It is not known if betamethasone dipropionate cream (augmented) passes into your breast milk. Breastfeeding women should use betamethasone dipropionate cream (augmented) on the smallest area of the skin and for the shortest time needed. Do not apply betamethasone dipropionate cream (augmented) directly to the nipple and areola to avoid contact with your baby.

Tell your healthcare provider about all the medicines you take,including prescription and over-the-counter medicines, vitamins, and herbal supplements.

Especiallytell your healthcare provider if you take other corticosteroid medicines by mouth or injection or use other products on your skin or scalp that contain corticosteroids.

Do not use other products containing a steroid medicine with betamethasone dipropionate cream (augmented) without talking to your healthcare provider first.

How should I use Betamethasone Dipropionate Cream (Augmented)?

- Use betamethasone dipropionate cream (augmented) exactly as your healthcare provider tells you to use it.
- Apply a thin layer (film) of betamethasone dipropionate cream (augmented) to the affected skin area 1 or 2 times each day. Do not use more than 50 grams of betamethasone dipropionate cream (augmented) in 1 week.
- Do not bandage, cover, or wrap the treated skin area unless your healthcare provider tells you to.
- Betamethasone dipropionate cream (augmented) should not be used to treat diaper rash or redness.
- Avoid using betamethasone dipropionate cream (augmented) on the face, groin, or underarms (armpits) or if thinning of the skin (atrophy) is present at the treatment site.
- Wash your hands after applying betamethasone dipropionate cream (augmented) unless you are using the medicine to treat your hands.

What are the possible side effects of Betamethasone Dipropionate Cream (Augmented)?

Betamethasone Dipropionate Cream (Augmented) may cause serious side effects, including:

- Betamethasone dipropionate cream (augmented) can pass through your skin.Too much betamethasone dipropionate cream (augmented) passing through your skin can cause your adrenal glands to stop working properly. Your healthcare provider may do blood tests to check for adrenal gland problems.
- Cushing's syndrome, a condition that happens when your body is exposed to too much of the hormone cortisol.
- High blood sugar(hyperglycemia).
- Effects on growth and weight in children.
- Vision problems.Topical corticosteroids including betamethasone dipropionate cream (augmented) may increase your chance of developing cataract(s) and glaucoma. Tell your healthcare provider if you develop blurred vision or other vision problems during treatment with betamethasone dipropionate cream (augmented).
- Skin problems.Skin problems including, allergic reactions (contact dermatitis) may happen during treatment with betamethasone dipropionate cream (augmented). Stop using betamethasone dipropionate cream (augmented) and tell your healthcare provider if you develop any skin reactions or have problems with healing during treatment with betamethasone dipropionate cream (augmented).

Your healthcare provider may do certain blood tests to check for side effects.

The most common side effect of betamethasone dipropionate cream (augmented) in adults includesstinging.

The most common side effects of betamethasone dipropionate cream (augmented) in children includethinning of the skin (atrophy), tiny red lines or blood vessels showing under the skin (telangiectasia), bruising and shininess.

These are not all of the possible side effects of betamethasone dipropionate cream (augmented).

Call your doctor for medical advice about side effects. You may report side effects to FDA at 1-800-FDA-1088.

How should I store Betamethasone Dipropionate Cream (Augmented)?

- Store betamethasone dipropionate cream (augmented) at room temperature between 68°F to 77°F (20°C to 25°C). Protect from freezing.
- Keep betamethasone dipropionate cream (augmented) and all medicines out of the reach of children.

General information about the safe and effective use of Betamethasone Dipropionate Cream (Augmented).

Medicines are sometimes prescribed for purposes other than those listed in a Patient Information leaflet. Do not use betamethasone dipropionate cream (augmented) for a condition for which it was not prescribed. Do not give betamethasone dipropionate cream (augmented) to other people, even if they have the same symptoms that you have. It may harm them. You can ask your pharmacist or healthcare provider for information about betamethasone dipropionate cream (augmented) that is written for health professionals.

What are the ingredients in Betamethasone Dipropionate Cream (Augmented)?

Active ingredient:betamethasone dipropionate

Inactive ingredients:carbomer homopolymer type C, ceteareth-30, chlorocresol, cyclomethicone, glyceryl oleate, propylene glycol, purified water, sodium hydroxide, sorbitol solution, white petrolatum and white wax.

Manufactured by: Sun Pharma Canada Inc., Brampton, Ontario, Canada L6T 1C1

Distributed by: Sun Pharmaceutical Industries, Inc.,Cranbury, NJ 08512

Revised: September 2025 5264297-0925-01 51

This Patient Information has been approved by the U.S. Food and Drug Administration.

Revised: 09/2025